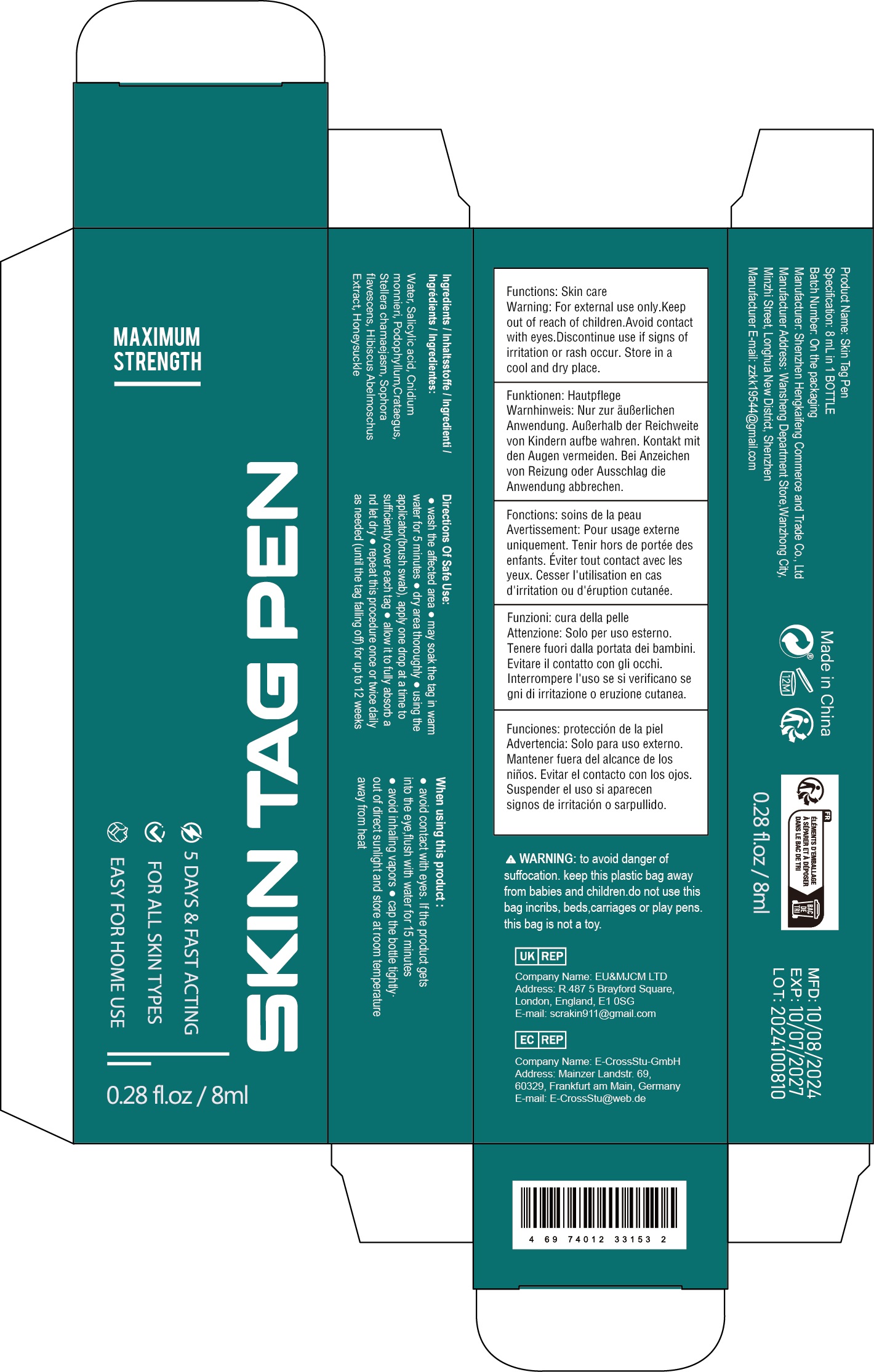 DRUG LABEL: Skin Tag Pen
NDC: 84117-037 | Form: LIQUID
Manufacturer: Shenzhen Hengkaifeng Commerce and Trade Co., Ltd
Category: otc | Type: HUMAN OTC DRUG LABEL
Date: 20241212

ACTIVE INGREDIENTS: SALICYLIC ACID 0.1 g/100 mL
INACTIVE INGREDIENTS: WATER

ACTIVE INGREDIENT

Salicylic acid

Purpose

Skin Tag Solution

Use

Skin Tag Solution

Warnings

For adult external use only. Flammable.
Keep away from heat or flame
Do not use
* Pregnant women and children.
* on open skin wounds

When using this product :

● avoid contact with eyes. If the product gets
into the eye,flush with water for 15 minutes
● avoid inhaling vapors ● cap the bottle tightly·
out of direct sunlight and store at room temperature
away from heat

Keep Out Of Reach Of Children

Directions Of Safe Use:

● wash the affected area ● may soak the tag in warm
water for 5 minutes ● dry area thoroughly ● using the
applicator(brush swab), apply one drop at a time to
sufficiently cover each tag ● allow it to fully absorb a
nd let dry ● repeat this procedure once or twice daily
as needed (until the tag falling off) for up to 12 weeks

Other information

Store between15-30C(59-86F)
Avoid freezing and excessive heat above
40C (104F)

Inactive ingredients

Water, Cnidium monnieri, Podophyllum,Crataegus, Stellera chamaejasm, Sophora flavescens, Hibiscus Abelmoschus Extract, Honeysuckle